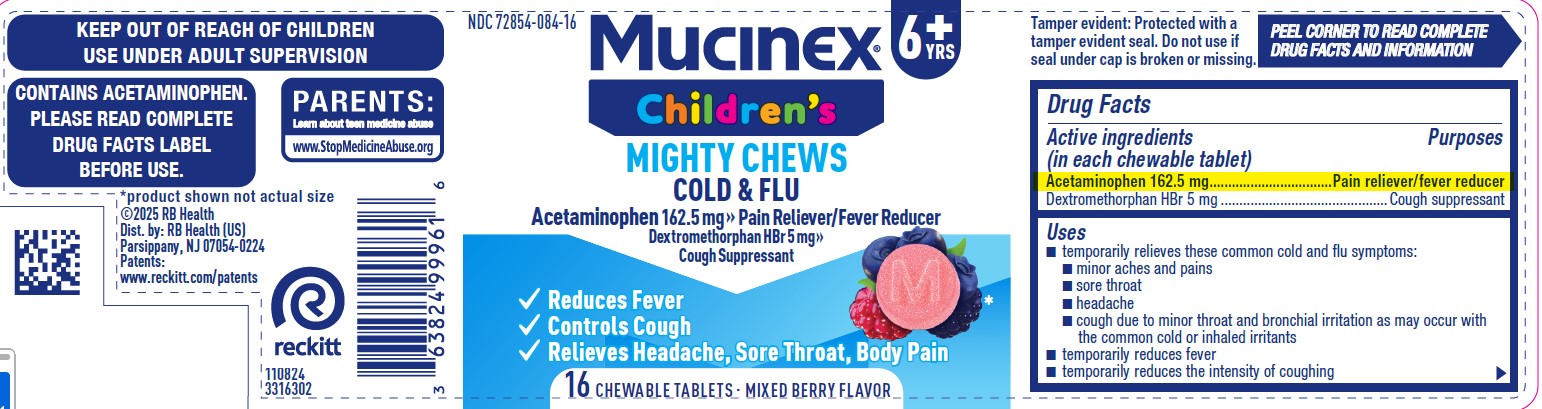 DRUG LABEL: Mucinex Childrens Mighty Chews Cold and Flu
NDC: 72854-084 | Form: TABLET, CHEWABLE
Manufacturer: RB Health (US) LLC
Category: otc | Type: HUMAN OTC DRUG LABEL
Date: 20250129

ACTIVE INGREDIENTS: ACETAMINOPHEN 162.5 mg/1 1; DEXTROMETHORPHAN HYDROBROMIDE 15 mg/1 1
INACTIVE INGREDIENTS: ETHYLCELLULOSE; CORN SYRUP; GLYCERIN; WATER; PECTIN; POTASSIUM SODIUM TARTRATE; SUCROSE; ANHYDROUS CITRIC ACID; ANHYDROUS TRISODIUM CITRATE; SUCRALOSE; MALIC ACID; MALTODEXTRIN; SODIUM CHLORIDE; SODIUM POLYMETAPHOSPHATE; FD&C RED NO. 40

Mucinex Children's Mighty Chews Cough

ACTIVE INGREDIENT

Dextromethorphan HBr 10 mg

PURPOSE

Dextromethorphan HBr 10 mg.......................... ...............Cough suppressant

Uses

■ temporarily relieves cough due to minor throat and bronchial irritation as
may occur with a cold

Warnings
Do not use
■ if you are now taking a prescription monoamine oxidase inhibitor (MAOI)
(certain drugs for depression, psychiatric, or emotional conditions, or
Parkinson’s disease), or for 2 weeks after stopping the MAOI drug. If you do not know if your prescription drug contains an MAOI, ask a doctor or pharmacist before taking this product.

Ask a doctor before use if you have
■ a sodium-restricted diet
■ persistent or chronic cough such as occurs with smoking, asthma, or emphysema
■ cough that occurs with too much phlegm (mucus)

When using this product
■ do not exceed recommended dosage

Stop use and ask a doctor if
■ cough lasts more than 7 days, comes back, or occurs with fever, rash, or
headache. These could be signs of a serious condition.

KEEP OUT OF REACH OF CHILDREN

If pregnant or breast-feeding, ask a health professional before use.

Keep out of reach of children. In case of overdose, get medical help or
contact a Poison Control Center right away

Directions

■ take every 4 hours or as directed by a doctor
■ chew thoroughly before swallowing

adults and children 12 years of age and over | 2 chewable tablets every 4 hours, not to exceed 12 chewable tablets in any 24-hour period
children 6 to under 12 years of age | 1 chewable tablet every 4 hours, not to exceed 6 chewable tablets in any 24-hour period
children under 6 years of age | do not use

Other information
■ each chewable tablet contains: potassium 5 mg and sodium 15 mg
■ store in a cool dry place at 20-25°C (68-77°F)

Inactive ingredients
anhydrous citric acid, corn syrup, FD&C red no. 40, flavors, glycerin, malic acid,
maltodextrin, pectin, potassium sodium tartrate, purified water, sodium chloride, trisodium citrate (anhydrous), sodium polymetaphosphate, sucralose, sucrose

Questions? 1-866-MUCINEX (1-866-682-4639)

PACKAGE LABEL

NDC 72854-084-016

Children's
Mucinex®

Cough Suppressant

Dextromethorphan HBr 5 mg

Age 6+

Mixed Berry Flavor

Chewable Tablets